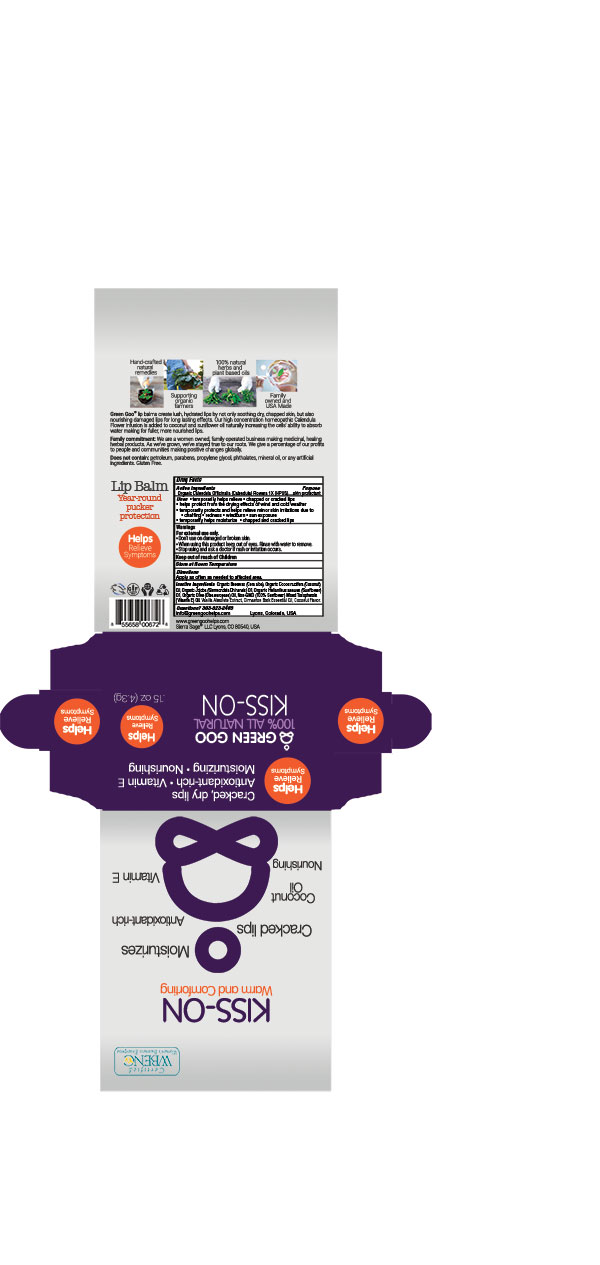 DRUG LABEL: Kiss-on Lip Balm
NDC: 70994-404 | Form: SALVE
Manufacturer: Sierra Sage Herbs LLC
Category: homeopathic | Type: HUMAN OTC DRUG LABEL
Date: 20170217

ACTIVE INGREDIENTS: CALENDULA OFFICINALIS FLOWER 1 [hp_X]/51.7 g
INACTIVE INGREDIENTS: YELLOW WAX; ALPHA-TOCOPHEROL; OLIVE OIL; SUNFLOWER OIL; JOJOBA OIL; COCONUT OIL; COCONUT; CINNAMON BARK OIL; VANILLA

Kiss-on Lip Balm

Purpose Section

Skin Protectant

Active Ingredients

Organic Calendula Officinalis (Calendula) Flowers 1X (HPUS)

Indications & Usage

• temporarily helps relieve • chapped or cracked lips
• helps protect from the drying effects of wind and cold weather
• temporarily protects and helps relieve minor skin irritations due to • chaffing • redness • windburn • sun exposure
• temporarily helps moisturize • chapped and cracked lips

Keep out of reach of children section

Keep out of reach of children.

Warnings Section

Warnings For external use only.

• Don’t use on damaged or broken skin.
• When using this product keep out of eyes. Rinse with water to remove.

• Stop using and ask a doctor if rash or irritation occurs.

Storage

Store at room temperature.

Dosage & Administration Section

Apply as often as needed to affected area.

Inactive Ingredients

Organic Beeswax (Cera alba), Organic Cocos nucifera (Coconut) Oil, Organic Jojoba (Simmondsia Chinensis) Oil, Organic Helianthus annuus (Sunflower) Oil, Organic Olive (Olea europaea) Oil, Non-GMO (100% Sunflower) Mixed Tocopherols (Vitamin E) Oil, Vanilla Absolute Extract, Cinnamon Bark Essential Oil, Coconut Flavor.